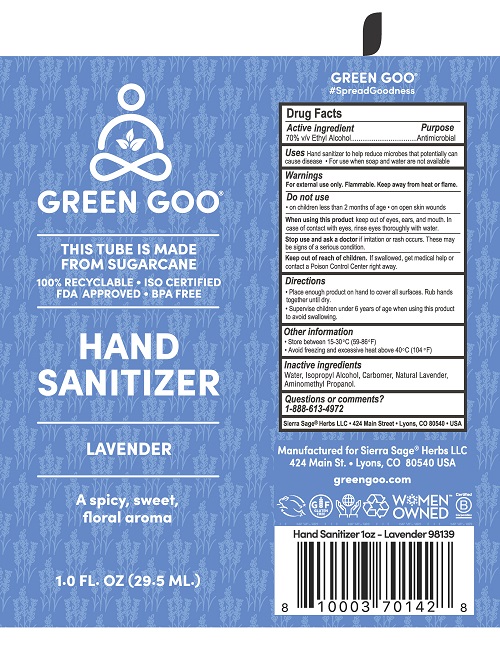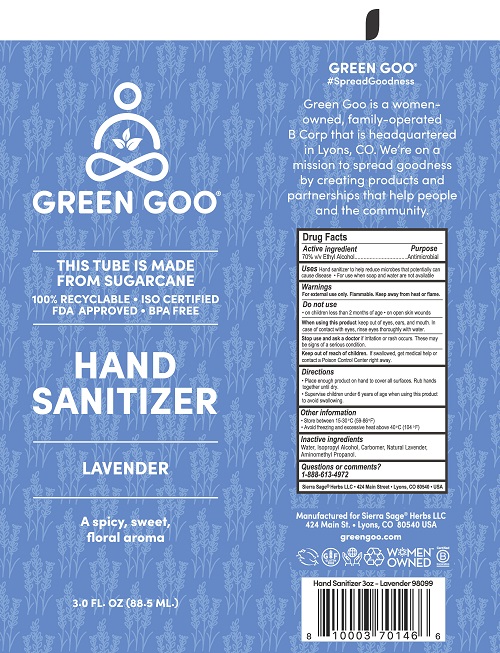 DRUG LABEL: Green Goo Hand Sanitizer
NDC: 70994-336 | Form: GEL
Manufacturer: Sierra Sage Herbs, LLC
Category: otc | Type: HUMAN OTC DRUG LABEL
Date: 20201119

ACTIVE INGREDIENTS: ALCOHOL 70 mL/100 mL
INACTIVE INGREDIENTS: LAVENDER OIL; ISOPROPYL ALCOHOL; AMINOMETHYLPROPANOL; CARBOMER 980; WATER

Green Goo - Natural Lavender

Active ingredient

70% v/v Ethyl Alcohol

Purpose

Antimicrobial

Uses

Hand sanitizer to help reduce microbes that potentially can cause disease

- For use when soap and water are not available

Warnings

For external use only. Flammable. Keep away from heat or flame.

Do not use

- on children less than 2 months of age
- on open skin wounds

When using this product keep out of eyes, ears, and mouth. In case of contact with eyes, rinse eyes thoroughly with water.

Stop use and ask a doctor if irritation or rash occurs. These may be signs of a serious condition.

Keep out of reach of children. If swallowed, get medical help or contact a Poison Control Center right away.

Directions

- Place enough product on hand to cover all surfaces. Rub hands together until dry.
- Supervise children under 6 years of age when using this product to avoid swallowing.

Other information

- Store between 15-30°C (59-86°F)
- Avoid freezing and excessive heat above 40°C (104°F)

Inactive ingredients

Water, Isopropyl Alcohol, Carbomer, Natural Lavender, Aminomethyl Propanol.

Questions or comments?

1-888-613-4972

Sierra Sage® Herbs LLC 424 Main Streen Lyons, CO 80540 USA

Principal Display Panel 3oz

GREEN GOO®

THIS TUBE IS MADE

FROM SUGARCANE

100% RECYCLABLE

ISO CERTIFIED

FDA APPROVED

BPA FREE

HAND SANITIZER

LAVENDER

A spicy, sweet, floral aroma

3.0 FL. OZ (88.5 ML.)

Principal Display Panel 1oz

GREEN GOO®

THIS TUBE IS MADE

FROM SUGARCANE

100% RECYCLABLE

ISO CERTIFIED

FDA APPROVED

BPA FREE

HAND SANITIZER

LAVENDER

A spicy, sweet, floral aroma

1.0 FL. OZ (29.5 ML.)